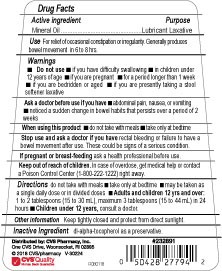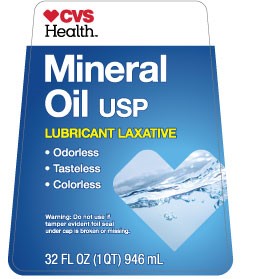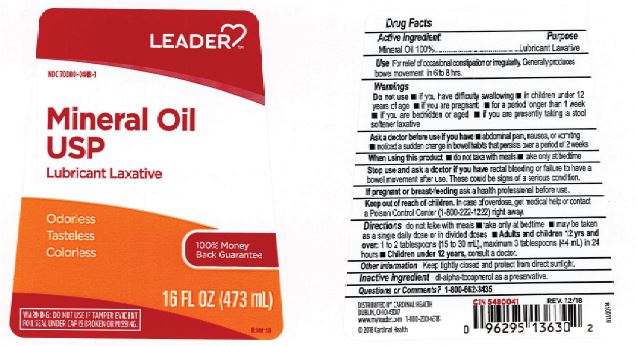 DRUG LABEL: Mineral Oil Heavy
NDC: 82645-906 | Form: LIQUID
Manufacturer: Pharma Nobis, LLC
Category: otc | Type: HUMAN OTC DRUG LABEL
Date: 20231222

ACTIVE INGREDIENTS: MINERAL OIL 1000 mg/1 mL
INACTIVE INGREDIENTS: .ALPHA.-TOCOPHEROL ACETATE, DL-

Private Label Mineral Oil Heavy

Drug Facts

Active ingredient

Mineral Oil Heavy

Purpose

Laxative

Use

For relief of occasional constipation or irregularit. Generally produces bowel movement in 6 to 8 hrs.

Warnings

Do not take this product if you have abdominal pain, nausea, vomiting, change in bowel habits persisting more than 2 weeks, rectal bleeding or kidney failure are present, or use for a period of longer than 1 week unless directed by a doctor. Frequent or prolonged use may result in the dependence on laxatives.

Do not administer to infants or young children, bedridden or aged patients unless directed by a doctor.

Ask a doctor before use if

you are currently taking a stool softener laxative.

If pregnant or brest feeding ask a health professional before use.

When using this Product discotinue use

and consult a doctor if there is a failure to have a bowel movement after use.

Keep out of reach of children

In case of accidental overdose, seek professional assistance or contact Poison Control Center immediately. In case of eye contact wash gently with water for 15 minutes.

Directions

Adults and children 12 yrs and older: 1 to 2 tablespoonfulls at bedtime.

Children 6 to 12 yrs. of age: 1 to 3 teaspoonfuls at bedtime.

Children under 6 yrs. of age: Consult a doctor before use.

Inactive ingredient

dl-alpha-tocopherol as a preservative.

Other information

Keep tightly closed and protect from direct light.